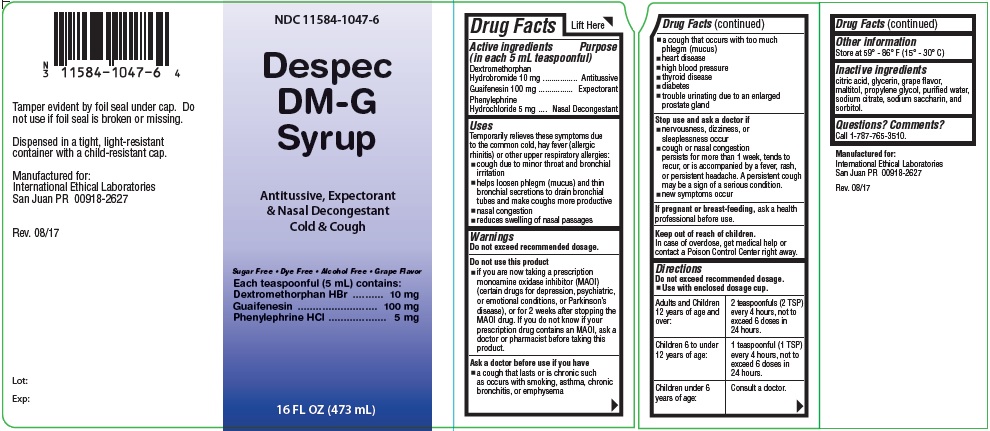 DRUG LABEL: DESPEC
NDC: 11584-1047 | Form: LIQUID
Manufacturer: INTERNATIONAL ETHICAL LABS
Category: otc | Type: HUMAN OTC DRUG LABEL
Date: 20181017

ACTIVE INGREDIENTS: DEXTROMETHORPHAN HYDROBROMIDE 10 mg/5 mL; PHENYLEPHRINE HYDROCHLORIDE 5 mg/5 mL; GUAIFENESIN 100 mg/5 mL
INACTIVE INGREDIENTS: GLYCERIN; MALTITOL; DIPROPYLENE GLYCOL

DESPEC DM-G

Active Ingredient

Active ingredients Purpose

(in each 5 mL teaspoonful)

Dextromethorphan

Hydrobromide 10 mg ................ Antitussive

Guaifenesin 100 mg ................ Expectorant

Phenylephrine

Hydrochloride 5 mg .... Nasal Decongestant

Purpose

Antitussive

Expectorant

Nasal Decongestant

Indications & Usage

Uses

Temporarily relieves these symptoms due

to the common cold, hay fever (allergic

rhinitis) or other upper respiratory allergies:

cough due to minor throat and bronchial

irritation

helps loosen phlegm (mucus) and thin

bronchial secretions to drain bronchial

tubes and make coughs more productive

nasal congestion

reduces swelling of nasal passages

Warnings

Do not exceed recommended dosage.

Do not use this product

if you are now taking a prescription

monoamine oxidase inhibitor (MAOI)

(certain drugs for depression, psychiatric,

or emotional conditions, or Parkinson’s

disease), or for 2 weeks after stopping the

MAOI drug. If you do not know if your

prescription drug contains an MAOI, ask a

doctor or pharmacist before taking this

product.

If pregnant or breast-feeding, ask a health

professional before use.

Ask a doctor before use if you have

a cough that lasts or is chronic such

as occurs with smoking, asthma, chronic

bronchitis, or emphysema.

a cough that occurs with too much

phlegm (mucus)

heart disease

high blood pressure

thyroid disease

diabetes

trouble urinating due to an enlarged

prostate gland

Stop use

Stop use and ask a doctor if

nervousness, dizziness, or

sleeplessness occur

cough or nasal congestion

persists for more than 1 week, tends to

recur, or is accompanied by a fever, rash,

or persistent headache. A persistent cough

may be a sign of a serious condition.

new symptoms occur

Keep out of reach of children

In case of overdose, get medical help or

contact a Poison Control Center right away.

Dosage & Administration

Do not exceed recommended dosage.

Use with enclosed dosage cup.

Adults and Children

12 years of age and

over:

Children 6 to under

12 years of age:

Children under 6

years of age:

2 teaspoonfuls (2 TSP)

every 4 hours, not to

exceed 6 doses in

24 hours.

1 teaspoonful (1 TSP)

every 4 hours, not to

exceed 6 doses in

24 hours.

Consult a doctor.

Other safety information

Other information

Store at 59° - 86° F (15° - 30° C)

Inactive ingredient

citric acid, glycerin, grape flavor,

maltitol, propylene glycol, purified water,

sodium citrate, sodium saccharin, and

sorbitol.

Questions? Comments?

Call 1-787-765-3510.

Manufactured for:

International Ethical Laboratories

San Juan PR 00918-2627

Manufactured by:

Woodfield Pharmaceutical, LLC

Houston, TX 77099

Rev. 09/15